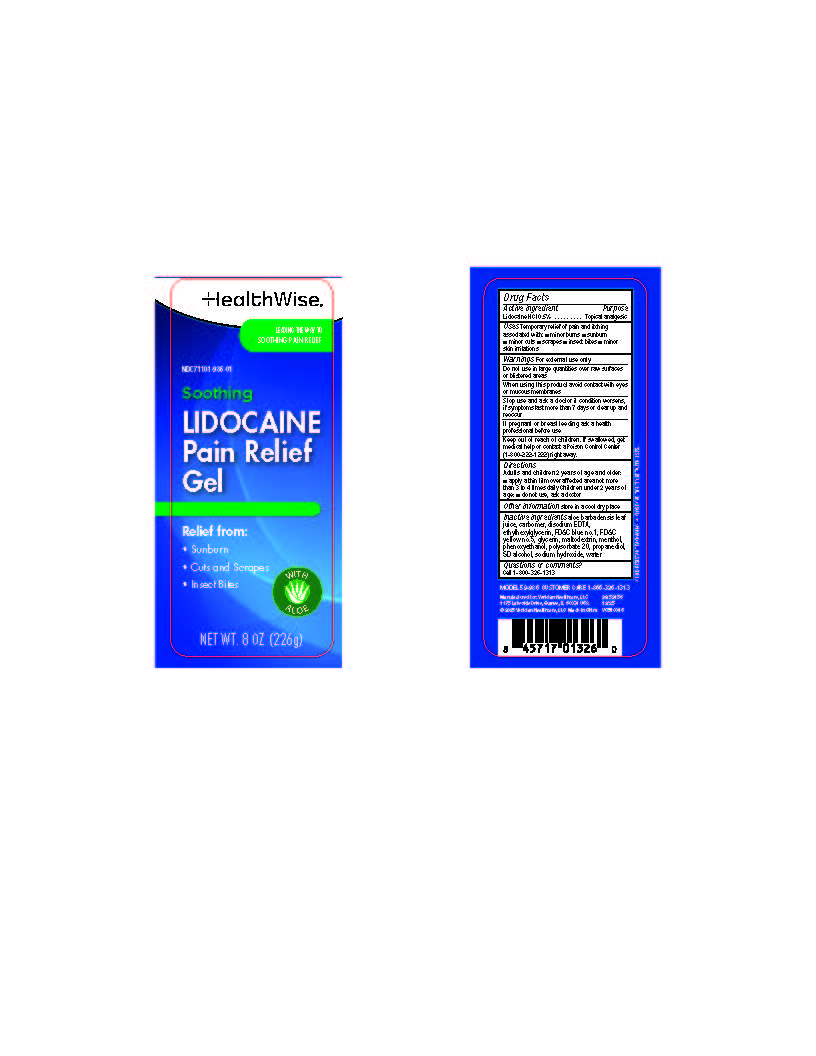 DRUG LABEL: HealthWise Soothing Lidocaine Pain Relief
NDC: 71101-986 | Form: GEL
Manufacturer: Veridian Healthcare
Category: otc | Type: HUMAN OTC DRUG LABEL
Date: 20260206

ACTIVE INGREDIENTS: LIDOCAINE HYDROCHLORIDE ANHYDROUS 0.5 g/1 g
INACTIVE INGREDIENTS: GLYCERIN; CARBOMER; PROPANEDIOL; FD&C BLUE NO. 1; ALCOHOL; PHENOXYETHANOL; LEVOMENTHOL; WATER; SODIUM HYDROXIDE; EDETATE DISODIUM; FD&C YELLOW NO. 5; POLYSORBATE 20; ETHYLHEXYLGLYCERIN; MALTODEXTRIN; ALOE BARBADENSIS LEAF JUICE

HealthWise Soothing Lidocaine Pain Relief Gel

Drug Facts

Active Ingredient

Lidocaine HCI 0.5%

Purpose

- Topical Analgesic

Uses

Uses Temporary relief of pain and itching associated with:

■ minor burns

■ sunburn
■ minor cuts

■ scrapes

■ insect bites

■ minor skin irritations

Warnings

For external use only

Directions

Adults and children 2 years of age and older: ■ apply a thin film over affected area not more than 3 to 4 times daily

Children under 2 years of age: ■ do not use, ask a doctor

Other information

- store in a cool dry place

Inactive ingredients

Aloe barbadensis leaf juice, carbomer, disodium EDTA, ethylhexylglycerin, FD&C blue no.1, FD&C yellow no.5, glycerin, maltodextrin, menthol, phenoxyethanol, polysorbate 20, propanediol, SD alcohol, sodium hydroxide, water

When using this product, do not

When using this product avoid contact with eyes or mucous membranes

Do not use in large quantities over raw surfaces or blistered areas

Stop use and ask a doctor if condition worsens, if symptoms last more than 7 days or clear up and reoccur

PREGNANCY OR BREAST FEEDING

If pregnant or breast-feeding,ask a health professional before use.

Keep out of reach of children. If swallowed, get medical help or contact a Poison Control Center (1-800-222-1222) right away.